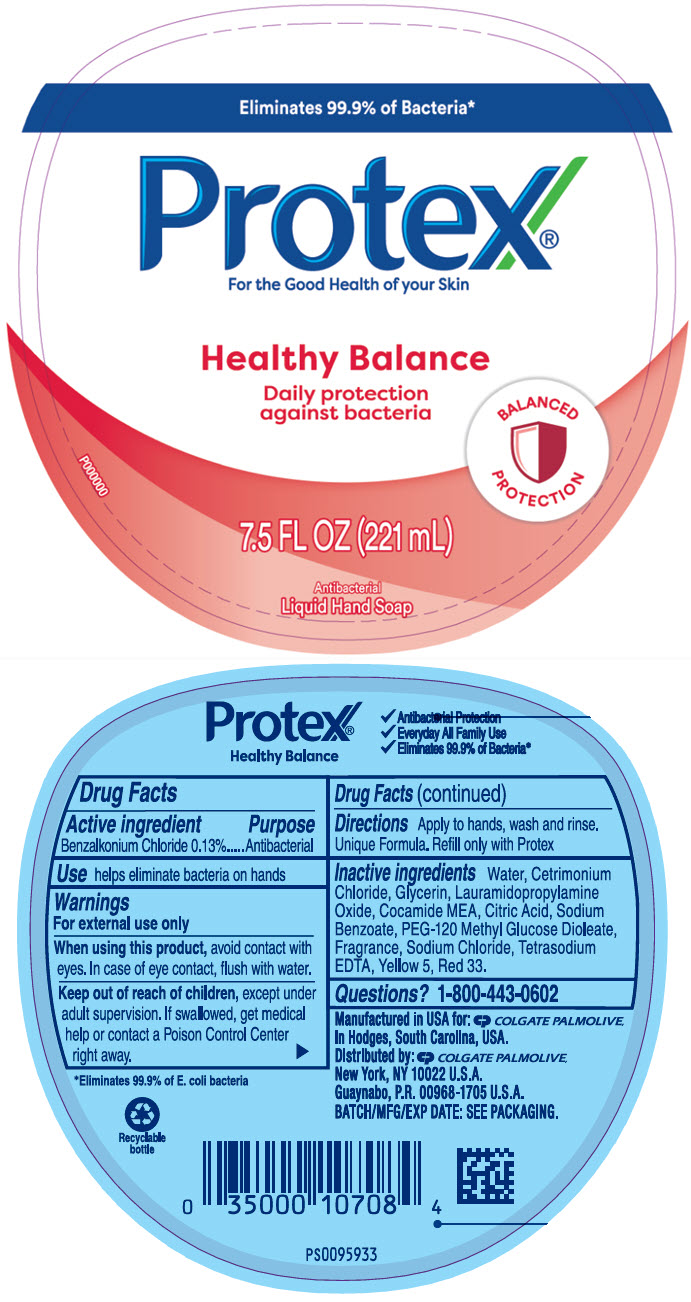 DRUG LABEL: Protex Balance antibacterial hand
NDC: 35000-255 | Form: LIQUID
Manufacturer: Colgate-Palmolive Company
Category: otc | Type: HUMAN OTC DRUG LABEL
Date: 20251124

ACTIVE INGREDIENTS: BENZALKONIUM CHLORIDE 1.33 mg/1 mL
INACTIVE INGREDIENTS: WATER; CETRIMONIUM CHLORIDE; GLYCERIN; LAURAMIDOPROPYLAMINE OXIDE; COCO MONOETHANOLAMIDE; ANHYDROUS CITRIC ACID; SODIUM BENZOATE; PEG-120 METHYL GLUCOSE DIOLEATE; SODIUM CHLORIDE; EDETATE SODIUM; FD&C YELLOW NO. 5; D&C RED NO. 33

Protex®

Drug Facts

Active ingredient

Benzalkonium chloride 0.13%

Purpose

Antibacterial

Use

helps eliminate bacteria on hands

Warnings

For external use only

When using this product, avoid contact with eyes. In case of eye contact, flush with water.

Keep out of reach of children, except under adult supervision. If swallowed, get medical help or contact a Poison Control Center right away.

Directions

Apply to hands, wash and rinse. Unique Formula. Refill only with Protex

Inactive ingredients

Water, Cetrimonium Chloride, Glycerin, Lauramidopropylamine Oxide, Cocamide MEA, Citric Acid, Sodium Benzoate, PEG-120 Methyl Glucose Dioleate, Fragrance, Sodium Chloride, Tetrasodium EDTA, Yellow 5, Red 33.

Questions?

1-800-443-0602

Distributed by:
COLGATE-PALMOLIVE COMPANY, Distr.
Guaynabo, P.R. 00968-1705

PRINCIPAL DISPLAY PANEL - 221 mL Bottle Label

Eliminates 99.9% of Bacteria*

Protex®

For the Good Health of your Skin

Healthy Balance

Daily protection
against bacteria

BALANCED
PROTECTION

P000000
7.5 FL OZ (221 mL)

Antibacterial
Liquid Hand Soap